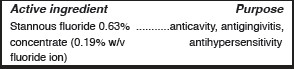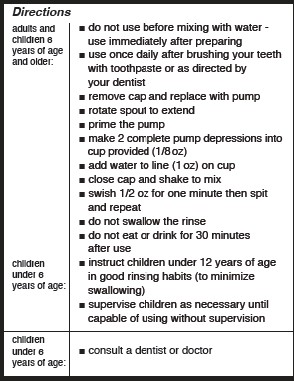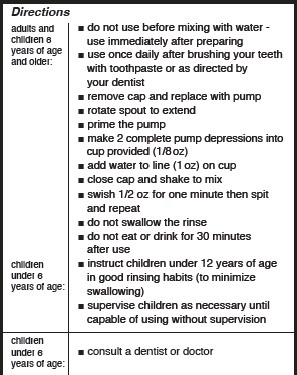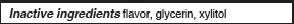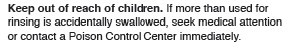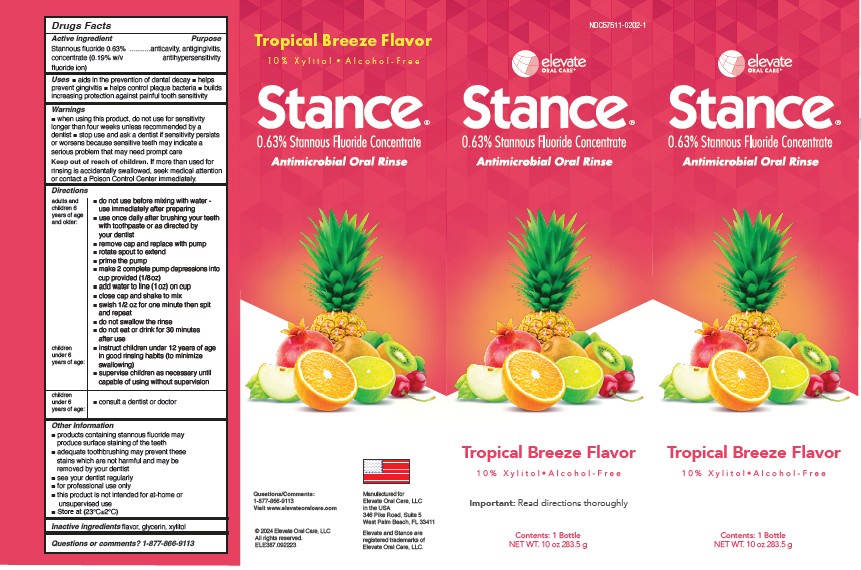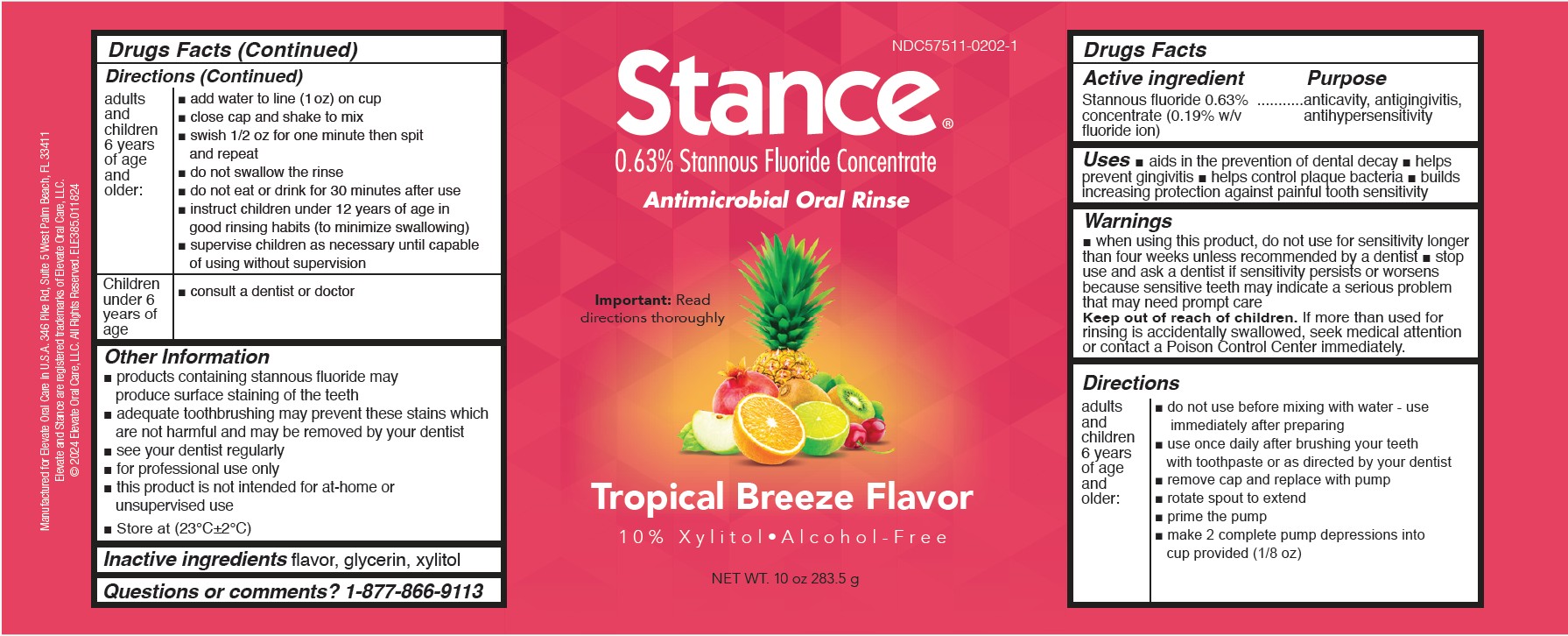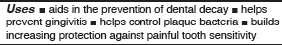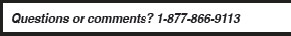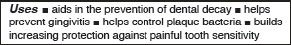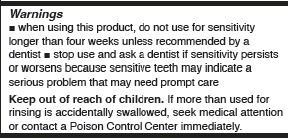 DRUG LABEL: Stance
NDC: 57511-0202 | Form: RINSE
Manufacturer: Elevate Oral Care
Category: otc | Type: HUMAN OTC DRUG LABEL
Date: 20250923

ACTIVE INGREDIENTS: STANNOUS FLUORIDE 1.2 mg/1 mL
INACTIVE INGREDIENTS: GLYCERIN; XYLITOL

Stance 0.63% Stannous Fluoride Concentrate Rinse Tropical Breeze